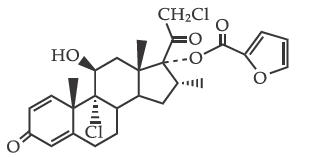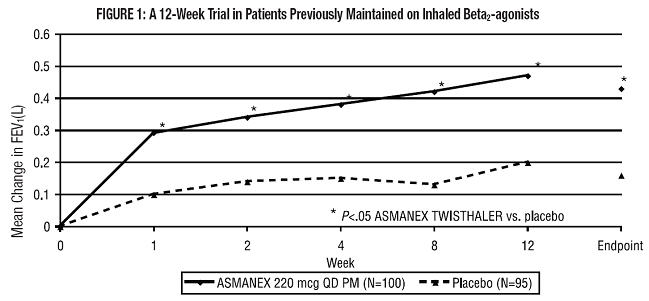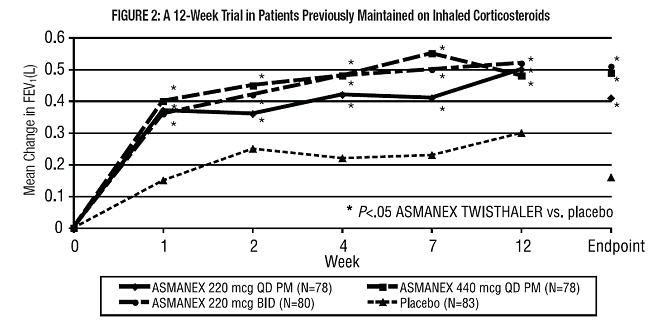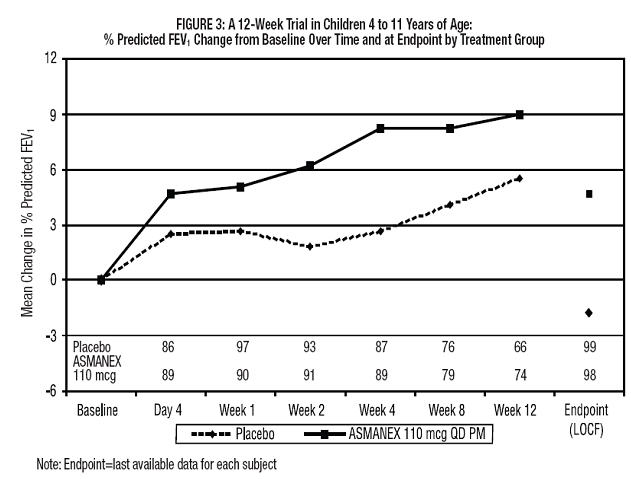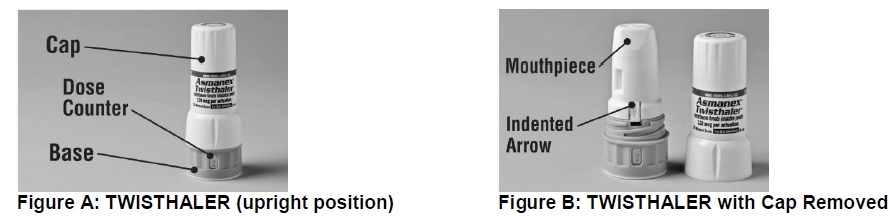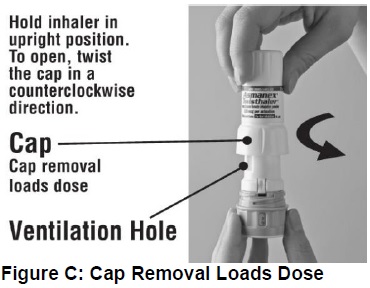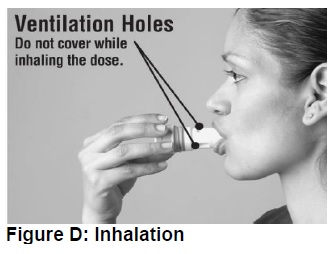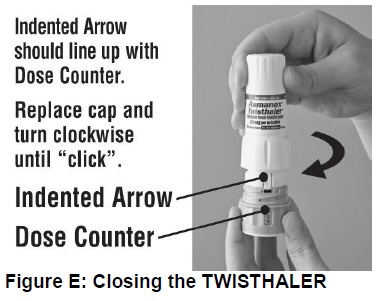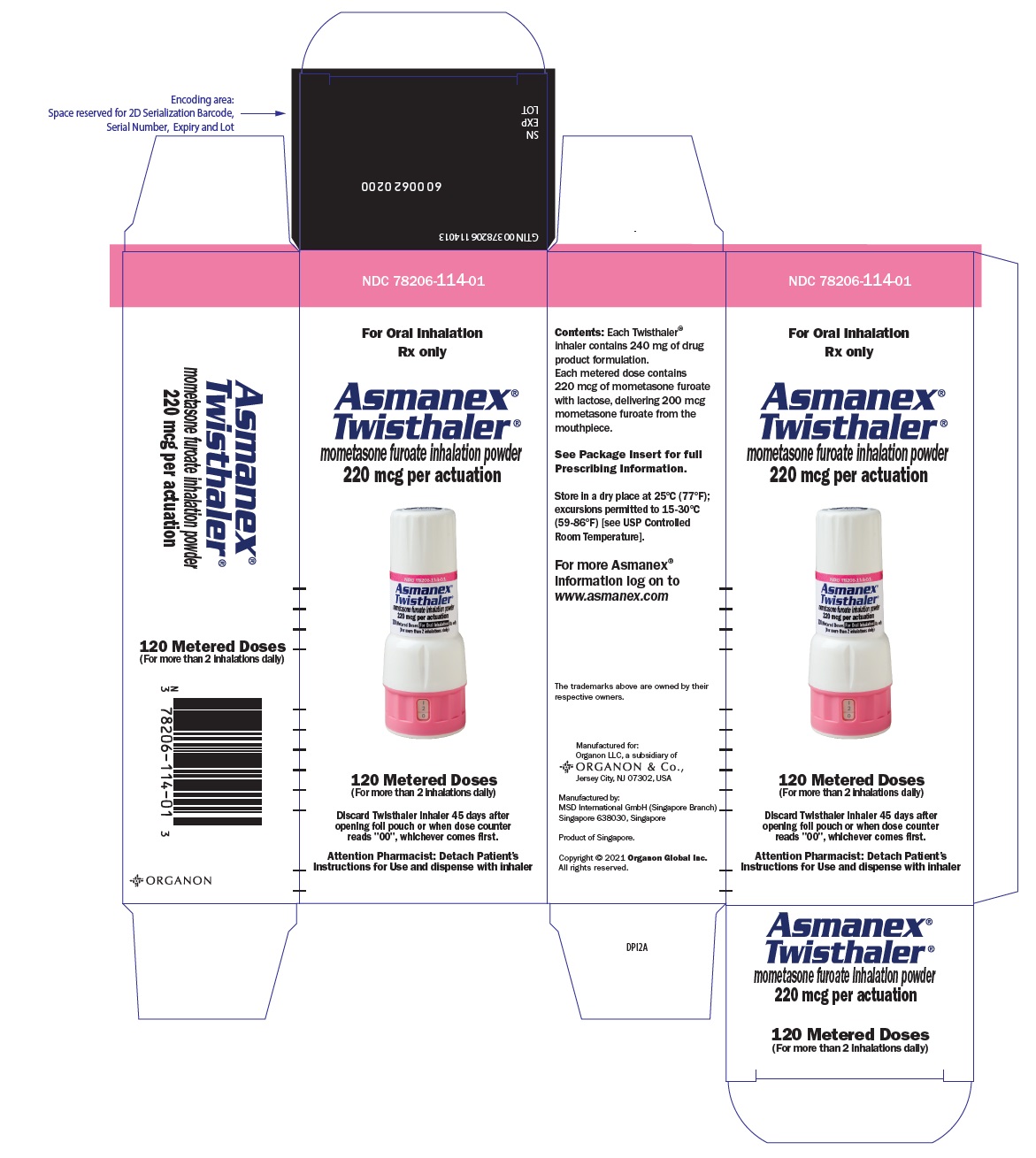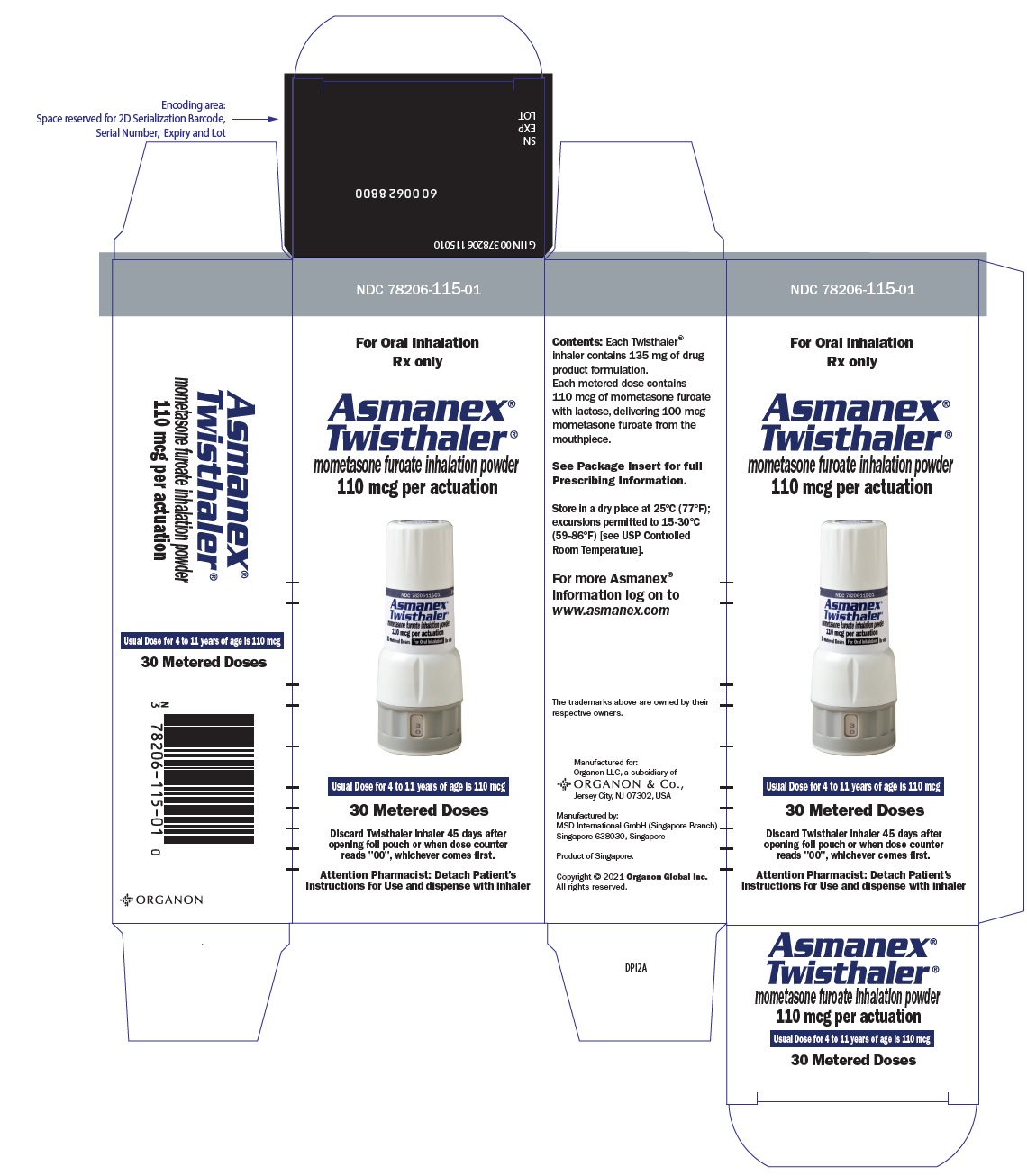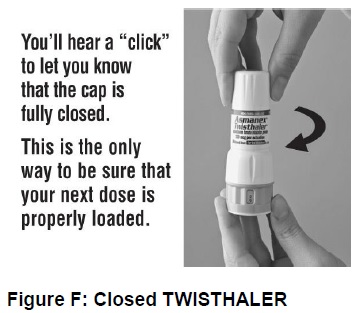 DRUG LABEL: ASMANEX
NDC: 78206-114 | Form: INHALANT
Manufacturer: Organon LLC
Category: prescription | Type: HUMAN PRESCRIPTION DRUG LABEL
Date: 20250211

ACTIVE INGREDIENTS: Mometasone Furoate 220 ug/1 1
INACTIVE INGREDIENTS: Anhydrous Lactose

HIGHLIGHTS OF PRESCRIBING INFORMATION

These highlights do not include all the information needed to use ASMANEX TWISTHALER safely and effectively. See full prescribing information for ASMANEX TWISTHALER.
ASMANEX® TWISTHALER® (mometasone furoate inhalation powder), for oral inhalation use
Initial U.S. Approval: 1987

RECENT MAJOR CHANGES

Dosage and Administration (2) | 02/2021
Warnings and Precautions (5.1, 5.2) | 02/2021

1 INDICATIONS AND USAGE

ASMANEX TWISTHALER is a corticosteroid indicated for maintenance treatment of asthma as prophylactic therapy in patients 4 years of age and older. (1)

Limitations of Use: ASMANEX TWISTHALER is not indicated for the relief of acute bronchospasm (1, 5.2) or in children less than 4 years of age (1, 8.4).

2 DOSAGE AND ADMINISTRATION

- For oral inhalation only. (2)
- Instruct patients to inhale rapidly and deeply and, after administration, rinse mouth with water and spit out contents without swallowing. (2)

Recommended Dosages for ASMANEX TWISTHALER Treatment
Previous Therapy | Recommended Starting Dose | Highest Recommended Daily Dose
Patients ≥12 years who received bronchodilators alone | 220 mcg once daily in the evening | 440 mcg
Patients ≥12 years who received inhaled corticosteroids | 220 mcg once daily in the evening | 440 mcg
Patients ≥12 years who received oral corticosteroids | 440 mcg twice daily | 880 mcg
Children 4-11 years of age | 110 mcg once daily in the evening | 110 mcg
,,,Please refer to section 2.1 for full dosage recommendations and details.

3 DOSAGE FORMS AND STRENGTHS

Inhalation powder:

- 220 mcg TWISTHALER: delivers 200 mcg mometasone furoate per actuation. (3)
- 110 mcg TWISTHALER: delivers 100 mcg mometasone furoate per actuation. (3)

4 CONTRAINDICATIONS

- Patients with status asthmaticus or other acute episodes of asthma where intensive measures are required. (4)
- Patients with a known hypersensitivity to milk proteins or any ingredients of ASMANEX TWISTHALER. (4)

5 WARNINGS AND PRECAUTIONS

- Candida albicans infection of the mouth and pharynx. Monitor patients periodically for signs of adverse effects in the mouth and pharynx. After administration, advise patients to rinse mouth with water and spit out contents without swallowing. (5.1)
- Deterioration of asthma or acute episodes: ASMANEX TWISTHALER should not be used for relief of acute symptoms. Patients require immediate re-evaluation during rapidly deteriorating asthma. (5.2)
- Hypersensitivity reactions including anaphylaxis, angioedema, pruritus, and rash have been reported with the use of ASMANEX TWISTHALER. Discontinue ASMANEX TWISTHALER if such reactions occur. (5.3)
- Potential worsening of existing tuberculosis; fungal, bacterial, viral, or parasitic infection; or ocular herpes simplex. More serious or even fatal course of chickenpox or measles in susceptible patients. Use caution in patients with the above because of the potential for worsening of these infections. (5.4)
- Risk of impaired adrenal function when transferring from oral steroids to inhaled corticosteroids. Taper patients slowly from systemic corticosteroids if transferring to ASMANEX TWISTHALER. (5.5)
- Hypercorticism, suppression of hypothalamic-pituitary-adrenal (HPA) function, with very high dosages or at the regular dosage in susceptible individuals. If such changes occur discontinue ASMANEX TWISTHALER slowly. (5.6)
- Reduction in bone mineral density with long-term administration. Monitor patients with major risk factors for decreased bone mineral content. (5.7)
- Suppression of growth in children. Monitor growth routinely in pediatric patients receiving ASMANEX TWISTHALER. (5.8)
- Glaucoma and cataracts. Consider referral to an ophthalmologist in patients who develop ocular symptoms or use ASMANEX TWISTHALER long term. (5.9)
- Paradoxical bronchospasm may occur with ASMANEX TWISTHALER. Treat bronchospasm immediately with a fast-acting inhaled bronchodilator and discontinue use of ASMANEX TWISTHALER. (5.10)
- Strong cytochrome P450 3A4 inhibitors (e.g., ritonavir): Risk of increased systemic corticosteroid effects. Exercise caution when used with ASMANEX TWISTHALER. (5.11)

6 ADVERSE REACTIONS

The most common adverse reactions (incidence ≥5%) are headache, allergic rhinitis, pharyngitis, upper respiratory tract infection, sinusitis, oral candidiasis, dysmenorrhea, musculoskeletal pain, back pain, and dyspepsia. (6.1)

To report SUSPECTED ADVERSE REACTIONS, contact Organon LLC, a subsidiary of Organon & Co., at 1-844-674-3200 or FDA at 1-800-FDA-1088 or www.fda.gov/medwatch.

7 DRUG INTERACTIONS

- Strong cytochrome P450 3A4 inhibitors (e.g., ritonavir): Use with caution. May cause increased systemic corticosteroid effects. (7.1)

FULL PRESCRIBING INFORMATION

1 INDICATIONS AND USAGE

ASMANEX® TWISTHALER® is indicated for the maintenance treatment of asthma as prophylactic therapy in adult and pediatric patients 4 years of age and older.

Limitations of Use

ASMANEX TWISTHALER is not indicated for the relief of acute bronchospasm.

ASMANEX TWISTHALER is not indicated in children less than 4 years of age.

2 DOSAGE AND ADMINISTRATION

Administration Information

Administer ASMANEX TWISTHALER by the orally inhaled route only. Instruct patients to inhale rapidly and deeply. After administration, advise patients to rinse the mouth with water and spit out contents without swallowing. Individual patients will experience a variable time to onset and degree of symptom relief. Maximum benefit may not be achieved for 1 to 2 weeks or longer after initiation of treatment. After asthma stability has been achieved, it is desirable to titrate to the lowest effective dosage to reduce the possibility of side effects. For patients ≥12 years of age who do not respond adequately to the starting dose after 2 weeks of therapy, higher doses may provide additional asthma control. The safety and efficacy of ASMANEX TWISTHALER when administered in excess of recommended doses have not been established.

2.1 Recommended Dosages in Adult and Pediatric Patients 4 Years of Age and Older

The recommended starting doses and highest recommended daily dose for ASMANEX TWISTHALER treatment based on prior asthma therapy are provided in Table 1.

Table 1: Recommended Dosages for ASMANEX TWISTHALER Treatment
Previous Therapy | Recommended Starting Dose | Highest Recommended Daily Dose
Patients ≥12 years who received bronchodilators alone | 220 mcg once daily in the evening [When administered once daily, ASMANEX TWISTHALER should be taken only in the evening.] | 440 mcg [The 440 mcg daily dose may be administered in divided doses of 220 mcg twice daily or as 440 mcg once daily.]
Patients ≥12 years who received inhaled corticosteroids | 220 mcg once daily in the evening | 440 mcg
Patients ≥12 years who received oral corticosteroids [For Patients Currently Receiving Chronic Oral Corticosteroid Therapy: Prednisone should be reduced no faster than 2.5 mg/day on a weekly basis, beginning after at least 1 week of ASMANEX TWISTHALER therapy. Monitor patients carefully for signs of asthma instability, including serial objective measures of airflow, and for signs of adrenal insufficiency during steroid taper and following discontinuation of oral corticosteroid therapy [see Warnings and Precautions (5.5)].] | 440 mcg twice daily | 880 mcg
Children 4-11 years of age [Recommended pediatric dosage is 110 mcg once daily in the evening regardless of prior therapy.] | 110 mcg once daily in the evening | 110 mcg

3 DOSAGE FORMS AND STRENGTHS

Inhalation powder:

- ASMANEX TWISTHALER 220 mcg delivers 200 mcg mometasone furoate per actuation from the mouthpiece.
- ASMANEX TWISTHALER 110 mcg delivers 100 mcg mometasone furoate per actuation from the mouthpiece.

4 CONTRAINDICATIONS

ASMANEX TWISTHALER is contraindicated:

- Status Asthmaticus: in the primary treatment of status asthmaticus or other acute episodes of asthma where intensive measures are required.
- Hypersensitivity: in patients with known hypersensitivity to milk proteins or any ingredients of ASMANEX TWISTHALER [see Warnings and Precautions (5.3) and Description (11)].

5 WARNINGS AND PRECAUTIONS

5.1 Oropharyngeal Candidiasis

In clinical trials, the development of localized infections of the mouth and pharynx with Candida albicans occurred in 195 of 3007 patients treated with ASMANEX TWISTHALER. If oropharyngeal candidiasis develops, it should be treated with appropriate local or systemic (i.e., oral) antifungal therapy while remaining on treatment with ASMANEX TWISTHALER therapy, but at times therapy with the ASMANEX TWISTHALER may need to be interrupted. After administration, advise patients to rinse the mouth with water and spit out contents without swallowing.

5.2 Acute Asthma Episodes

ASMANEX TWISTHALER is not a bronchodilator and is not indicated for rapid relief of bronchospasm or other acute episodes of asthma. A short acting beta2-agonist, such as albuterol, should be available at all times to treat acute asthma symptoms. Instruct patients to contact their physician immediately if episodes of asthma that are not responsive to bronchodilators occur during the course of treatment with ASMANEX TWISTHALER. During such episodes, patients may require therapy with oral corticosteroids.

5.3 Hypersensitivity Reactions Including Anaphylaxis

Hypersensitivity reactions including rash, pruritus, angioedema, and anaphylactic reaction have been reported with use of ASMANEX TWISTHALER. Discontinue ASMANEX TWISTHALER if such reactions occur [see Contraindications (4) and Adverse Reactions (6.2)].

ASMANEX TWISTHALER contains small amounts of lactose, which contains trace levels of milk proteins. In postmarketing experience with ASMANEX TWISTHALER, anaphylactic reactions in patients with milk protein allergy have been reported [see Contraindications (4) and Adverse Reactions (6.2)].

5.4 Immunosuppression and Risk of Infections

Persons who are using drugs that suppress the immune system are more susceptible to infections than healthy individuals. Chickenpox and measles, for example, can have a more serious or even fatal course in susceptible children or adults using corticosteroids. In such children or adults who have not had these diseases or who are not properly immunized, particular care should be taken to avoid exposure. How the dose, route, and duration of corticosteroid administration affect the risk of developing a disseminated infection is not known. The contribution of the underlying disease and/or prior corticosteroid treatment to the risk is also not known. If exposed to chickenpox, prophylaxis with varicella zoster immune globulin (VZIG) may be indicated. If exposed to measles, prophylaxis with pooled intramuscular immunoglobulin (IG) may be indicated. (See the respective package inserts for complete VZIG and IG prescribing information.) If chickenpox develops, treatment with antiviral agents may be considered.

Inhaled corticosteroids should be used with caution, if at all, in patients with active or quiescent tuberculosis infection of the respiratory tract; untreated systemic fungal, bacterial, viral, or parasitic infections; or ocular herpes simplex.

5.5 Transferring Patients from Systemic Corticosteroid Therapy

HPA Suppression/Adrenal Insufficiency

Particular care is needed for patients who are transferred from systemically active corticosteroids to ASMANEX TWISTHALER because deaths due to adrenal insufficiency have occurred in asthmatic patients during and after transfer from systemic corticosteroids to less systemically available inhaled corticosteroids. After withdrawal from systemic corticosteroids, a number of months are required for recovery of hypothalamic-pituitary-adrenal (HPA) function.

Patients who have been previously maintained on 20 mg or more per day of prednisone (or its equivalent) may be most susceptible, particularly when their systemic corticosteroids have been almost completely withdrawn. During this period of HPA suppression, patients may exhibit signs and symptoms of adrenal insufficiency when exposed to trauma, surgery, or infection (particularly gastroenteritis) or other conditions associated with severe electrolyte loss. Although ASMANEX TWISTHALER may improve control of asthma symptoms during these episodes, in recommended doses it supplies less than normal physiological amounts of corticosteroid systemically and does NOT provide the mineralocorticoid activity necessary for coping with these emergencies.

During periods of stress or severe asthma attack, patients who have been withdrawn from systemic corticosteroids should be instructed to resume oral corticosteroids (in large doses) immediately and to contact their physicians for further instruction. These patients should also be instructed to carry a medical identification card indicating that they may need supplementary systemic corticosteroids during periods of stress or severe asthma attack.

Patients requiring oral corticosteroids should be weaned slowly from systemic corticosteroid use after transferring to ASMANEX TWISTHALER. Prednisone reduction can be accomplished by reducing the daily prednisone dose by 2.5 mg on a weekly basis during treatment with ASMANEX TWISTHALER [see Dosage and Administration (2.1)]. Lung function (FEV1 or PEFR), beta-agonist use, and asthma symptoms should be carefully monitored during withdrawal of oral corticosteroids. In addition to monitoring asthma signs and symptoms, patients should be observed for signs and symptoms of adrenal insufficiency such as fatigue, lassitude, weakness, nausea and vomiting, and hypotension.

Unmasking of Allergic Conditions Previously Suppressed by Systemic Corticosteroids

Transfer of patients from systemic corticosteroid therapy to ASMANEX TWISTHALER may unmask allergic conditions previously suppressed by the systemic corticosteroid therapy, e.g., rhinitis, conjunctivitis, eczema, arthritis, and eosinophilic conditions.

Corticosteroid Withdrawal Symptoms

During withdrawal from oral corticosteroids, some patients may experience symptoms of systemically active corticosteroid withdrawal, e.g., joint and/or muscular pain, lassitude, and depression, despite maintenance or even improvement of respiratory function.

5.6 Hypercorticism and Adrenal Suppression

ASMANEX TWISTHALER will often help control asthma symptoms with less suppression of HPA function than therapeutically similar oral doses of prednisone. Since individual sensitivity to effects on cortisol production exists, physicians should consider this information when prescribing ASMANEX TWISTHALER. Particular care should be taken in observing patients postoperatively or during periods of stress for evidence of inadequate adrenal response. It is possible that systemic corticosteroid effects such as hypercorticism and adrenal suppression may appear in a small number of patients, particularly when ASMANEX TWISTHALER is administered at higher than recommended doses over prolonged periods of time. If such effects occur, the dosage of ASMANEX TWISTHALER should be reduced slowly, consistent with accepted procedures for reducing systemic corticosteroids and for management of asthma.

5.7 Reduction in Bone Mineral Density

Decreases in bone mineral density (BMD) have been observed with long-term administration of products containing inhaled corticosteroids, including mometasone furoate. The clinical significance of small changes in BMD with regard to long-term outcomes is unknown. Patients with major risk factors for decreased bone mineral content, such as prolonged immobilization, family history of osteoporosis, or chronic use of drugs that can reduce bone mass (e.g., anticonvulsants and corticosteroids) should be monitored and treated with established standards of care.

In a 2-year double-blind study in 103 male and female asthma patients 18 to 50 years of age previously maintained on bronchodilator therapy (baseline FEV1 85%–88% predicted), treatment with ASMANEX TWISTHALER 220 mcg twice daily resulted in significant reductions in lumbar spine (LS) BMD at the end of the treatment period compared to placebo. The mean change from baseline to endpoint in the lumbar spine BMD was -0.015 (-1.43%) for the ASMANEX TWISTHALER group compared to 0.002 (0.25%) for the placebo group. In another 2-year double-blind study in 87 male and female asthma patients 18 to 50 years of age previously maintained on bronchodilator therapy (baseline FEV1 82%–83% predicted), treatment with ASMANEX TWISTHALER 440 mcg twice daily demonstrated no statistically significant changes in lumbar spine BMD at the end of the treatment period compared to placebo. The mean change from baseline to endpoint in the lumbar spine BMD was -0.018 (-1.57%) for the ASMANEX TWISTHALER group compared to -0.006 (-0.43%) for the placebo group.

5.8 Effect on Growth

Orally inhaled corticosteroids, including ASMANEX TWISTHALER, may cause a reduction in growth velocity when administered to pediatric patients. Monitor the growth of pediatric patients receiving ASMANEX TWISTHALER routinely (e.g., via stadiometry). To minimize the systemic effects of orally inhaled corticosteroids, including ASMANEX TWISTHALER, titrate each patient's dose to the lowest dosage that effectively controls his/her symptoms [see Use in Specific Populations (8.4)].

5.9 Glaucoma and Cataracts

In clinical trials, glaucoma, increased intraocular pressure, and cataracts have been reported in 8 of 3007 patients following the administration of ASMANEX TWISTHALER. Consider referral to an ophthalmologist in patients who develop ocular symptoms or use ASMANEX TWISTHALER long term.

5.10 Paradoxical Bronchospasm

As with other inhaled asthma medications, bronchospasm may occur with an immediate increase in wheezing after dosing. If bronchospasm occurs following dosing with ASMANEX TWISTHALER, it should be treated immediately with a fast-acting inhaled bronchodilator.

Treatment with ASMANEX TWISTHALER should be discontinued and alternative therapy instituted.

5.11 Drug Interactions with Strong Cytochrome P450 3A4 Inhibitors

Caution should be exercised when considering the coadministration of ASMANEX TWISTHALER with ketoconazole, and other known strong CYP3A4 inhibitors (e.g., ritonavir, cobicistat-containing products, atazanavir, clarithromycin, indinavir, itraconazole, nefazodone, nelfinavir, saquinavir, telithromycin) because adverse effects related to increased systemic exposure to mometasone furoate may occur [see Drug Interactions (7.1) and Clinical Pharmacology (12.3)].

6 ADVERSE REACTIONS

The following clinically significant adverse reactions are described elsewhere in the labeling:

- Oropharyngeal Candidiasis [see Warnings and Precautions (5.1)]
- Immunosuppression and Risk of Infections [see Warnings and Precautions (5.4)]
- Hypercorticism and Adrenal Suppression [see Warnings and Precautions (5.6)]
- Reduction in Bone Mineral Density [see Warnings and Precautions (5.7)]
- Growth Effects [see Warnings and Precautions (5.8) and Use in Specific Populations (8.4)]
- Glaucoma and Cataracts [see Warnings and Precautions (5.9)]

6.1 Clinical Studies Experience

The safety data described below reflect exposure to ASMANEX TWISTHALER in 2380 patients with asthma exposed for 8 to 12 weeks and 627 patients with asthma exposed for 1 year in a total of 17 clinical trials.

In adult and adolescent patients 12 years of age and older, ASMANEX TWISTHALER was studied in 10 placebo-controlled clinical trials of 8 to 12 weeks duration with a total of 1750 patients receiving ASMANEX TWISTHALER. There were also 3 trials with a total of 475 patients receiving ASMANEX TWISTHALER for 1 year. In the 8- to 12-week clinical trials, the population was 12 to 83 years of age; 38% males and 62% females; and 83% Caucasian, 8% black, 6% Hispanic, and 3% other race/ethnicity. Patients received ASMANEX TWISTHALER 110 mcg twice daily (n=133), 220 mcg once daily in the morning (n=209), 220 mcg once daily in the evening (n=232), 220 mcg twice daily (n=433), 440 mcg once daily in the morning (n=419), 440 mcg once daily in the evening (n=250), or 440 mcg twice daily (n=74). In 3 long-term safety trials (two 9-month extensions of efficacy trials and one 52-week active-controlled safety trial), 475 patients with asthma (12-83 years of age, 44% males, 56% females, 87% Caucasian, 8% black, 4% Hispanic, and 1% other race/ethnicity) received various doses of ASMANEX TWISTHALER for 1 year.

In pediatric patients 4 to 11 years of age, ASMANEX TWISTHALER was studied in 3 placebo-controlled clinical trials of 12 weeks duration with a total of 630 patients receiving ASMANEX TWISTHALER and a 52-week, active-controlled safety trial with a total of 152 patients receiving ASMANEX TWISTHALER. In the 12-week clinical trials, the population was 4 to 11 years of age; 63% males and 37% females; and 67% Caucasian, 13% black, 17% Hispanic, and 3% other race/ethnicity. Patients received ASMANEX TWISTHALER 110 mcg once daily in the evening (n=98), 110 mcg once daily in the morning (n=181), 110 mcg twice daily (n=179), or 220 mcg once daily in the morning (n=172). In the long-term active-controlled safety trial (n=152), patients with asthma (4 to 11 years of age, 60% males and 40% females, 84% Caucasian, 11% Black, and 5% Hispanic) received ASMANEX TWISTHALER 110 mcg twice daily or 220 mcg once daily in the morning for 52 weeks.

Because clinical trials are conducted under widely varying conditions, adverse reaction rates observed in the clinical trials of a drug cannot be directly compared to rates in the clinical trials of another drug and may not reflect the rates observed in practice.

Adults and Adolescents 12 Years of Age and Older: The safety results of the 10 trials that were 8 to 12 weeks in duration were pooled because patients with asthma in these studies were previously maintained on bronchodilators and/or inhaled corticosteroids. The safety results of the one 12-week clinical trial in patients with asthma previously treated with oral corticosteroids are presented separately.

In the pooled 8- to 12-week clinical trials, adverse reactions were reported in 70% of patients treated with ASMANEX TWISTHALER (n=1750) compared to 65% of patients taking placebo (n=720). Table 2 displays the common adverse reactions (≥3% in any patient group receiving ASMANEX TWISTHALER) that occurred more frequently in patients treated with ASMANEX TWISTHALER compared to patients treated with placebo.

Table 2: Adverse Reactions with ≥3% Incidence in 10 Controlled Clinical Trials with ASMANEX TWISTHALER in Patients 12 Years of Age and Older Previously on Bronchodilators and/or Inhaled Corticosteroids
 | (%) of Patients
 | ASMANEX TWISTHALER
Adverse Reaction | 220 mcg twice daily (n=433) | 440 mcg once daily (n=497) | 220 mcg once daily in the evening (n=232) | Placebo (n=720)
Adverse Reaction | Headache | 22 | 17 | 20 | 20
Allergic Rhinitis | 15 | 11 | 14 | 13
Pharyngitis | 11 | 8 | 13 | 7
Upper Respiratory Infection | 10 | 8 | 15 | 7
Sinusitis | 6 | 6 | 5 | 5
Candidiasis, oral | 6 | 4 | 4 | 2
Dysmenorrhea [Percentages are based on the number of female patients.] | 9 | 4 | 4 | 4
Musculoskeletal Pain | 8 | 4 | 4 | 5
Back Pain | 6 | 3 | 3 | 4
Dyspepsia | 5 | 3 | 3 | 3
Myalgia | 3 | 2 | 3 | 2
Abdominal Pain | 3 | 2 | 3 | 2
Nausea | 3 | 1 | 3 | 2
Average Duration of Exposure (Days) | 81 | 70 | 80 | 62

The following other adverse reactions occurred in these clinical trials with an incidence of at least 1% but less than 3% and were more common on ASMANEX TWISTHALER therapy than on placebo:

Body as a Whole: fatigue, flu-like symptoms, pain

Gastrointestinal: gastroenteritis, vomiting, anorexia

Hearing, Vestibular: earache

Resistance Mechanism: infection

Respiratory: dysphonia, epistaxis, nasal irritation, respiratory disorder, throat dry

In the 12-week trial in adult asthmatics who previously required oral corticosteroids, the effects of ASMANEX TWISTHALER therapy administered as two 220-mcg inhalations twice daily (n=46) were compared with those of placebo (n=43). Adverse reactions, whether considered drug-related or not by the investigators, reported in more than 3 patients in the ASMANEX TWISTHALER treatment group, and which occurred more frequently than in placebo were (ASMANEX TWISTHALER % vs. placebo %): musculoskeletal pain (22% vs. 14%), oral candidiasis (22% vs. 9%), sinusitis (22% vs. 19%), allergic rhinitis (20% vs. 5%), upper respiratory infection (15% vs. 14%), arthralgia (13% vs. 7%), fatigue (13% vs. 2%), depression (11% vs. 0%), and sinus congestion (9% vs. 0%). In considering these data, an increased duration of exposure for patients on ASMANEX TWISTHALER treatment (77 days vs. 58 days on placebo) should be taken into account.

Long-Term Clinical Trials Experience - 12 Years of Age and Older: In 3 long-term safety trials, 475 patients with asthma 12 years of age and older were treated with ASMANEX TWISTHALER 220 mcg twice daily (n=60), 220 mcg once daily in the morning (n=41), 220 mcg once daily in the evening (n=40), 440 mcg once daily in the morning (n=44), 440 mcg once daily in the evening (n=41), 440 mcg twice daily (n=62), 880 mcg once daily (n=59), or at variable doses (n=128) for 52 weeks. The safety profile of ASMANEX TWISTHALER in the 52-week trials was similar to the findings in the 8- to 12-week clinical trials. In patients previously on inhaled corticosteroids, cataracts were reported in 3 patients (0.9%) treated with ASMANEX TWISTHALER, compared to 1 patient (1.7%) treated with the active comparator medication. Increased ocular pressure at the end of the study was observed in 2 patients, both on ASMANEX TWISTHALER 880 mcg once daily in the morning. Oral candidiasis, dysphonia, and dysmenorrhea were seen at a higher frequency with long-term administration than in the 8- to 12-week trials.

Pediatric Patients 4 to 11 Years of Age: In the three 12-week clinical trials in pediatric patients 4 to 11 years of age, patients with asthma were previously maintained on bronchodilators and/or inhaled corticosteroids. The safety results from 1 trial are described in Table 3 for ASMANEX TWISTHALER 110 mcg once daily in the evening. The safety results from the other 2 trials showed similar findings.

Overall adverse reactions were reported with approximately the same frequency by patients treated with ASMANEX TWISTHALER and those receiving placebo. Table 3 displays the common adverse reactions (≥2% in any patient group receiving ASMANEX TWISTHALER) that occurred more frequently in patients 4 to 11 years of age treated with ASMANEX TWISTHALER compared with placebo-treated patients.

Table 3: Adverse Reactions with ≥2% Incidence in a 12-Week Study with ASMANEX TWISTHALER in Patients 4 to 11 Years of Age Previously on Bronchodilators and/or Inhaled Corticosteroids
 | (%) of Patients
 | ASMANEX TWISTHALER
Adverse Reaction | 110 mcg once daily in the evening (n=98) | Placebo (n=99)
Fever | 7 | 5
Allergic Rhinitis | 4 | 3
Abdominal Pain | 6 | 2
Vomiting | 3 | 2
Urinary Tract Infection | 2 | 1
Bruise | 2 | 0
Average Duration of Exposure (Days) | 72 | 68

Long-Term Clinical Trials Experience in Children 4 to 11 Years of Age: In a 52-week, active-controlled, long-term safety trial, 152 patients with asthma 4 to 11 years of age were treated with ASMANEX TWISTHALER 110 mcg twice daily (n=74) or 220 mcg once daily (n=78). The safety profile for ASMANEX TWISTHALER in the 52-week trial was similar to the findings in the 12-week clinical trials.

6.2 Postmarketing Experience

The following adverse reactions have been reported during post-approval use of ASMANEX TWISTHALER. Because they are reported voluntarily from a population of uncertain size, it is not always possible to reliably estimate their frequency or establish a causal relationship to drug exposure.

Eye disorders: Vision blurred [see Warnings and Precautions (5.9)].

Immune System Disorders: Immediate and delayed hypersensitivity reactions including rash, pruritus, angioedema and anaphylactic reaction [see Warnings and Precautions (5.3) and Contraindications (4)].

Respiratory, Thoracic and Mediastinal Disorders: Asthma aggravation, which may include cough, dyspnea, wheezing and bronchospasm.

7 DRUG INTERACTIONS

In clinical studies, the concurrent administration of ASMANEX TWISTHALER and other drugs commonly used in the treatment of asthma was not associated with any unusual adverse reactions.

7.1 Inhibitors of Cytochrome P450 3A4

Concomitant administration of CYP3A4 inhibitors may inhibit the metabolism of, and increase the systemic exposure to, mometasone furoate and potentially increase the risk for systemic corticosteroid side effects [see Clinical Pharmacology (12.3)]. Caution should be exercised when considering the coadministration of ASMANEX TWISTHALER with long-term ketoconazole and other known strong CYP3A4 inhibitors (e.g., ritonavir, cobicistat-containing products, atazanavir, clarithromycin, indinavir, itraconazole, nefazodone, nelfinavir, saquinavir, telithromycin). Consider the benefit of coadministration versus the potential risk of systemic corticosteroid effects, in which case patients should be monitored for systemic corticosteroid side effects.

8 USE IN SPECIFIC POPULATIONS

8.1 Pregnancy

Risk Summary

There are no adequate and well-controlled studies of ASMANEX TWISTHALER in pregnant women. There are clinical considerations with the use of ASMANEX TWISTHALER in pregnant women [see Clinical Considerations]. In animal reproduction studies with pregnant mice, rats, or rabbits, mometasone furoate caused increased fetal malformations and decreased fetal survival and growth following administration of doses that produced exposures approximately 1/3 to 8 times the maximum recommended human dose (MRHD) on a mcg/m^2 or AUC basis [see Data]. However, experience with oral corticosteroids suggests that rodents are more prone to teratogenic effects from corticosteroid exposure than humans.

The estimated background risk of major birth defects and miscarriage for the indicated population is unknown. In the U.S. general population, the estimated risk of major birth defects and miscarriage in clinically recognized pregnancies is 2 to 4% and 15 to 20%, respectively.

Clinical Considerations

Disease-associated maternal and/or embryo/fetal risk

In women with poorly or moderately controlled asthma, there is an increased risk of several perinatal adverse outcomes such as preeclampsia in the mother and prematurity, low birth weight, and small for gestational age in the neonate. Pregnant women with asthma should be closely monitored and medication adjusted as necessary to maintain optimal asthma control.

Data

Animal Data

In an embryofetal development study with pregnant mice dosed throughout the period of organogenesis, mometasone furoate produced cleft palate at an exposure approximately 1/3 of the MRHD (on a mcg/m^2 basis with maternal subcutaneous doses of 60 mcg/kg and above) and decreased fetal survival at an exposure approximately equivalent to the MRHD (on a mcg/m^2 basis with a maternal subcutaneous dose of 180 mcg/kg). No toxicity was observed with a dose that produced an exposure approximately 1/10 of the MRHD (on a mcg/m^2 basis with maternal topical dermal doses of 20 mcg/kg and above).

In an embryofetal development study with pregnant rats dosed throughout the period of organogenesis, mometasone furoate produced fetal umbilical hernia at exposures approximately 6 times the MRHD (on a mcg/m^2 basis with maternal topical dermal doses of 600 mcg/kg and above) and delays in fetal ossification at exposures approximately 3 times the MRHD (on a mcg/m^2 basis with maternal topical dermal doses of 300 mcg/kg and above).

In another reproductive toxicity study, pregnant rats were dosed with mometasone furoate throughout pregnancy or late in gestation. Treated animals had prolonged and difficult labor, fewer live births, lower birth weight, and reduced early pup survival at an exposure that was approximately 6 times the MRHD (on an area under the curve (AUC) basis with a maternal subcutaneous dose of 15 mcg/kg). There were no findings with an exposure approximately 3 times the MRHD (on an AUC basis with a maternal subcutaneous dose of 7.5 mcg/kg).

Embryofetal development studies were conducted with pregnant rabbits dosed with mometasone furoate by either the topical dermal route or oral route throughout the period of organogenesis. In the study using the topical dermal route, mometasone furoate caused multiple malformations in fetuses (e.g., flexed front paws, gallbladder agenesis, umbilical hernia, hydrocephaly) at an exposure approximately 3 times the MRHD (on a mcg/m^2 basis with maternal topical dermal doses of 150 mcg/kg and above). In the study using the oral route, mometasone furoate caused increased fetal resorptions and cleft palate and/or head malformations (hydrocephaly and domed head) at an exposure approximately 1/2 of the MRHD (on an AUC basis with a maternal oral dose of 700 mcg/kg). At an exposure approximately 2 times the MRHD (on an AUC basis with a maternal oral dose of 2800 mcg/kg), most litters were aborted or resorbed. No effects were observed at an exposure approximately 1/10 of the MRHD (on an AUC basis with a maternal oral dose of 140 mcg/kg).

8.2 Lactation

Risk Summary

There are no available data on the presence of ASMANEX TWISTHALER in human milk, the effects on the breastfed child, or the effects on milk production. Other inhaled corticosteroids, similar to mometasone furoate, are present in human milk. The developmental and health benefits of breastfeeding should be considered along with the mother's clinical need for ASMANEX TWISTHALER and any potential adverse effects on the breastfed infant from ASMANEX TWISTHALER or from the underlying maternal condition.

8.4 Pediatric Use

The safety and effectiveness of ASMANEX TWISTHALER for maintenance treatment of asthma as prophylactic therapy have been established in children 4 years of age and older. Use of ASMANEX TWISTHALER in pediatric patients 12 years of age and older is supported by evidence from adequate and well-controlled clinical trials in this patient population [see Clinical Studies (14.1) and Adverse Reactions (6.1)].

Use of ASMANEX TWISTHALER in pediatric patients 4 to 11 years of age is supported by evidence from adequate and well-controlled clinical trials of 12 weeks duration in 630 patients 4 to 11 years of age receiving ASMANEX TWISTHALER and one 52-week safety trial in 152 patients [see Clinical Studies (14.1) and Adverse Reactions (6.1)].

Controlled clinical studies have shown that inhaled corticosteroids may cause a reduction in growth in pediatric patients. In these studies, the mean reduction in growth velocity was approximately 1 cm per year (range: 0.3–1.8 per year) and appears to depend upon dose and duration of exposure. This effect was observed in the absence of laboratory evidence of HPA axis suppression, suggesting that growth velocity is a more sensitive indicator of systemic corticosteroid exposure in pediatric patients than some commonly used tests of HPA axis function. The long-term effects of this reduction in growth velocity associated with orally inhaled corticosteroids, including the impact on final adult height, are unknown. The potential for "catch-up" growth following discontinuation of treatment with orally inhaled corticosteroids has not been adequately studied. The growth of children and adolescents (4 years of age and older) receiving orally inhaled corticosteroids, including ASMANEX TWISTHALER, should be monitored routinely (e.g., via stadiometry).

A 52-week, placebo-controlled, parallel-group study was conducted to assess the potential growth effects of ASMANEX TWISTHALER in 187 prepubescent children (131 males and 56 females) 4 to 9 years of age with asthma who were previously maintained on an inhaled beta-agonist. Treatment groups included ASMANEX TWISTHALER 110 mcg twice daily (n=44), 220 mcg once daily in the morning (n=50), 110 mcg once daily in the morning (n=48), and placebo (n=45). For each patient, an average growth rate was determined using an individual regression approach. The mean growth rates, expressed as least-squares mean in cm per year, for ASMANEX TWISTHALER 110 mcg twice daily, 220 mcg once daily in the morning, 110 mcg once daily in the morning, and placebo were 5.34, 5.93, 6.15, and 6.44, respectively. The differences from placebo and the corresponding 2-sided 95% CI of growth rates for ASMANEX TWISTHALER 110 mcg twice daily, 220 mcg once daily in the morning, and 110 mcg once daily in the morning were -1.11 (95% CI: -2.34, 0.12), -0.51 (95% CI: -1.69, 0.67), and -0.30 (95% CI: -1.48, 0.89), respectively.

The potential growth effects of prolonged treatment with orally inhaled corticosteroids should be weighed against clinical benefits obtained and the availability of safe and effective noncorticosteroid treatment alternatives. To minimize the systemic effects of orally inhaled corticosteroids, including ASMANEX TWISTHALER, each patient should be titrated to his/her lowest effective dose.

8.5 Geriatric Use

A total of 175 patients 65 years of age and over (23 of whom were 75 years of age and older) have been treated with ASMANEX TWISTHALER in controlled clinical trials. No overall differences in safety or effectiveness were observed between these and younger patients, and other reported clinical experience has not identified differences in responses between the elderly and younger patients, but greater sensitivity of some older individuals cannot be ruled out.

8.6 Hepatic Impairment

Concentrations of mometasone furoate appear to increase with severity of hepatic impairment [see Clinical Pharmacology (12.3)].

10 OVERDOSAGE

Chronic overdosage may result in signs/symptoms of hypercorticism [see Warnings and Precautions (5.6)]. Because of low systemic bioavailability and an absence of acute drug-related systemic findings in clinical studies, acute overdose is unlikely to require any treatment other than observation.

11 DESCRIPTION

Mometasone furoate, the active component of the ASMANEX TWISTHALER product, is a corticosteroid with the chemical name 9,21-dichloro-11(Beta),17-dihydroxy-16(alpha)-methylpregna-1,4-diene-3,20-dione 17-(2-furoate) and the following chemical structure:

Mometasone furoate is a white powder with an empirical formula of C27H30Cl2O6, and molecular weight of 521.44 Daltons.

The ASMANEX TWISTHALER 110 mcg and 220 mcg products are cap-activated, inhalation-driven, multidose dry powder inhalers containing mometasone furoate and anhydrous lactose (which contains trace amounts of milk proteins).

Each actuation of the ASMANEX TWISTHALER 110 mcg or 220 mcg inhaler provides a measured dose of approximately 0.75 or 1.5 mg mometasone furoate inhalation powder, containing 110 or 220 mcg of mometasone furoate, respectively. This results in delivery of 100 or 200 mcg mometasone furoate from the mouthpiece, respectively, based on in vitro testing at flow rates of 30 L/min and 60 L/min with constant volume of 2 L. The amount of mometasone furoate emitted from the inhaler in vitro does not differ significantly for flow rates ranging from 28.3 L/min to 70 L/min at a constant volume of 2 L. However, the amount of drug delivered to the lung will depend on patient factors such as inspiratory flow and peak inspiratory flow through the device. In adult and adolescent patients (aged ≥12 years) with varied asthma severity, mean peak inspiratory flow rate through the device was 69 L/min (range: 54–77 L/min). In pediatric patients (aged 5-12 years) diagnosed with asthma, mean peak inspiratory flow rate in the 5- to 8-year-old subgroup was >50 L/min (minimum of 46 L/min) and for the 9- to 12-year-old subgroup was >60 L/min (minimum of 48 L/min).

12 CLINICAL PHARMACOLOGY

12.1 Mechanism of Action

Mometasone furoate is a corticosteroid demonstrating potent anti-inflammatory activity. The precise mechanism of corticosteroid action on asthma is not known. Inflammation is an important component in the pathogenesis of asthma. Corticosteroids have been shown to have a wide range of inhibitory effects on multiple cell types (e.g., mast cells, eosinophils, neutrophils, macrophages, and lymphocytes) and mediators (e.g., histamine, eicosanoids, leukotrienes, and cytokines) involved in inflammation and in the asthmatic response. These anti-inflammatory actions of corticosteroids may contribute to their efficacy in asthma.

Mometasone furoate has been shown in vitro to exhibit a binding affinity for the human glucocorticoid receptor, which is approximately 12 times that of dexamethasone, 7 times that of triamcinolone acetonide, 5 times that of budesonide, and 1.5 times that of fluticasone. The clinical significance of these findings is unknown.

Though effective for the treatment of asthma, corticosteroids do not affect asthma symptoms immediately. Maximum improvement in symptoms following inhaled administration of mometasone furoate may not be achieved for 1 to 2 weeks or longer after starting treatment. When corticosteroids are discontinued, asthma stability may persist for several days or longer.

12.2 Pharmacodynamics

Adrenal Function: The effects of ASMANEX TWISTHALER on adrenal function have been evaluated in 2 clinical studies: 1 in adults 18 years of age and older and 1 in pediatric patients 6 to 11 years of age. Both clinical studies were specifically designed to assess the effect of ASMANEX TWISTHALER on adrenal function.

In a 29-day, randomized, double-blind, placebo-controlled study in 64 adult and adolescent patients 18 years of age and older with asthma, ASMANEX TWISTHALER 440 mcg twice daily and 880 mcg twice daily (twice the highest recommended daily dose) were compared to both placebo and prednisone 10 mg once daily as a positive control. The 30-minute post-Cosyntropin stimulation serum cortisol concentration on Day 29 was 23.2 mcg/dL for the ASMANEX 440 mcg twice daily group (n=16) and 20.8 mcg/dL for the ASMANEX 880 mcg twice daily group (n=16), compared to 14.5 mcg/dL for the oral prednisone 10-mg group (n=16) and 25 mcg/dL for the placebo group (n=16). The difference between ASMANEX 880 mcg twice daily (twice the maximum recommended dose) and placebo was statistically significant.

In a 29-day, randomized, double-blind, placebo-controlled, parallel-group clinical trial in 50 pediatric patients 6 to 11 years of age with asthma, ASMANEX TWISTHALER 110 mcg twice daily, 220 mcg twice daily, and 440 mcg twice daily (2-8 times the highest pediatric daily recommended daily dose) were compared to placebo. HPA-axis function was assessed by 12-hour plasma cortisol AUC and 24-hour urinary-free cortisol concentrations. After 29 days of treatment, the mean changes in plasma cortisol AUC0–12h from baseline were -0.11, -19.5, -21.3, and -3.47 mcg•hr/dL for the treatment groups of ASMANEX TWISTHALER 110 mcg twice daily (n=12), 220 mcg twice daily (n=12), 440 mcg twice daily (n=11), and placebo (n=7), respectively. The mean differences from placebo in the groups treated with ASMANEX TWISTHALER 110 mcg twice daily, 220 mcg twice daily, and 440 mcg twice daily were 3.4 mcg•hr/dL (95% CI: -14.0, 20.7), -16.0 mcg•hr/dL (95% CI: -33.9, 1.9), and -17.9 mcg•hr/dL (95% CI: -35.8, 0.0), respectively. For 24-hour urinary-free cortisol, after 29 days of treatment, the mean changes from baseline were -1.53, -1.33, -6.70, and -4.68 mcg/day for the groups treated with ASMANEX TWISTHALER 110 mcg twice daily (n=12), 220 mcg twice daily (n=12), 440 mcg twice daily (n=12), and placebo (n=10), respectively. The mean differences in urinary-free cortisol changes from baseline compared to placebo were 3.1 mcg/day (95% CI: -3.3, 9.6), 3.3 mcg/day (95% CI: -3.0, 9.7), and -2.0 mcg/day (95% CI: -8.6, 4.6) for the groups treated with 110 mcg twice daily, 220 mcg twice daily, and 440 mcg twice daily, respectively.

12.3 Pharmacokinetics

Absorption: Following a 1000 mcg inhaled dose of tritiated mometasone furoate inhalation powder to 6 healthy human subjects, plasma concentrations of unchanged mometasone furoate were shown to be very low compared to the total radioactivity in plasma. Following an inhaled single 400 mcg dose of ASMANEX TWISTHALER treatment to 24 healthy subjects, plasma concentrations for most subjects were near or below the lower limit of quantitation for the assay (50 pcg/mL). The mean absolute systemic bioavailability of the above single inhaled 400 mcg dose, compared to an intravenous 400 mcg dose of mometasone furoate, was determined to be less than 1%. Following administration of the recommended highest inhaled dose (400 mcg twice daily) to 64 patients for 28 days, concentration-time profiles were discernible, but with large intersubject variability. The coefficient of variation for Cmax and AUC ranged from approximately 50% to 100%. The mean peak plasma concentrations at steady state ranged from approximately 94 to 114 pcg/mL and the mean time to peak levels ranged from approximately 1.0 to 2.5 hours.

Distribution: Based on the study employing a 1000 mcg inhaled dose of tritiated mometasone furoate inhalation powder in humans, no appreciable accumulation of mometasone furoate in the red blood cells was found. Following an intravenous 400 mcg dose of mometasone furoate, the plasma concentrations showed a biphasic decline, with a mean terminal half-life of about 5 hours and the mean steady-state volume of distribution of 152 L. The in vitro protein binding for mometasone furoate was reported to be 98% to 99% (in a concentration range of 5–500 ng/mL).

Elimination:

Metabolism: Studies have shown that mometasone furoate is primarily and extensively metabolized in the liver of all species investigated and undergoes extensive metabolism to multiple metabolites. In vitro studies have confirmed the primary role of CYP3A4 in the metabolism of this compound; however, no major metabolites were identified.

Excretion: Following an intravenous dosing, the terminal half-life was reported to be about 5 hours. Following the inhaled dose of tritiated 1000 mcg mometasone furoate, the radioactivity is excreted mainly in the feces (a mean of 74%), and to a small extent in the urine (a mean of 8%) up to 7 days. No radioactivity was associated with unchanged mometasone furoate in the urine.

Specific Populations:

Pharmacokinetics have not been adequately investigated with ASMANEX TWISTHALER by gender, race or in pediatric patients.

Patients with Hepatic Impairment: Administration of a single inhaled dose of 400 mcg mometasone furoate to subjects with mild (n=4), moderate (n=4), and severe (n=4) hepatic impairment resulted in only 1 or 2 subjects in each group having detectable peak plasma concentrations of mometasone furoate (ranging from 50–105 pcg/mL). The observed peak plasma concentrations appear to increase with severity of hepatic impairment; however, the numbers of detectable levels were few.

Patients with Renal Impairment: The effects of renal impairment on mometasone furoate pharmacokinetics have not been adequately investigated.

Drug Interaction Studies: Inhibitors of Cytochrome P450 3A4: In a drug interaction study, an inhaled dose of mometasone furoate 400 mcg was given to 24 healthy subjects twice daily for 9 days and ketoconazole 200 mg (as well as placebo) were given twice daily concomitantly on Days 4 to 9. Mometasone furoate plasma concentrations were <150 pcg/mL on Day 3 prior to coadministration of ketoconazole or placebo. Following concomitant administration of ketoconazole, 4 out of 12 subjects in the ketoconazole treatment group (n=12) had peak plasma concentrations of mometasone furoate >200 pcg/mL on Day 9 (211–324 pcg/mL).

13 NONCLINICAL TOXICOLOGY

13.1 Carcinogenesis, Mutagenesis, Impairment of Fertility

In a 2-year carcinogenicity study in Sprague Dawley® rats, mometasone furoate demonstrated no statistically significant increase in the incidence of tumors at inhalation doses up to 67 mcg/kg (approximately 8 times the maximum recommended daily inhalation dose in adults on an AUC basis and 2 times the maximum recommended daily inhalation dose in pediatric patients based on an mcg/m^2 basis). In a 19-month carcinogenicity study in Swiss CD-1 mice, mometasone furoate demonstrated no statistically significant increase in the incidence of tumors at inhalation doses up to 160 mcg/kg (approximately 10 times the maximum recommended daily inhalation dose in adults on an AUC basis and 2 times the maximum recommended daily inhalation dose in pediatric patients based on an mcg/m^2 basis).

Mometasone furoate increased chromosomal aberrations in an in vitro Chinese hamster ovary cell assay, but did not have this effect in an in vitro Chinese hamster lung cell assay. Mometasone furoate was not mutagenic in the Ames test or mouse lymphoma assay, and was not clastogenic in an in vivo mouse micronucleus assay, a rat bone marrow chromosomal aberration assay, or a mouse male germ-cell chromosomal aberration assay. Mometasone furoate also did not induce unscheduled DNA synthesis in vivo in rat hepatocytes.

In reproductive studies in rats, impairment of fertility was not produced by subcutaneous doses up to 15 mcg/kg (approximately 6 times the maximum recommended daily inhalation dose in adults on an AUC basis).

13.2 Animal Toxicology and/or Pharmacology

Reproductive Toxicology Studies: In mice, mometasone furoate caused cleft palate at subcutaneous doses of 60 mcg/kg and above (less than the maximum recommended daily inhalation dose in adults on an mcg/m^2 basis). Fetal survival was reduced at 180 mcg/kg (approximately equal to the maximum recommended daily inhalation dose in adults on an mcg/m^2 basis). No toxicity was observed at 20 mcg/kg (less than the maximum recommended daily inhalation dose in adults on an mcg/m^2 basis).

In rats, mometasone furoate produced umbilical hernia at topical dermal doses of 600 mcg/kg and above (approximately 6 times the maximum recommended daily inhalation dose in adults on an mcg/m^2 basis). A dose of 300 mcg/kg (approximately 3 times the maximum recommended daily inhalation dose in adults on an mcg/m^2 basis) produced delays in ossification but no malformations.

When rats received subcutaneous doses of mometasone furoate throughout pregnancy or during the later stages of pregnancy, 15 mcg/kg (approximately 6 times the maximum recommended daily inhalation dose in adults on an AUC basis) caused prolonged and difficult labor and reduced the number of live births, birth weight, and early pup survival. Similar effects were not observed at 7.5 mcg/kg (approximately 3 times the maximum recommended daily inhalation dose in adults on an AUC basis).

In rabbits, mometasone furoate caused multiple malformations (e.g., flexed front paws, gallbladder agenesis, umbilical hernia, hydrocephaly) at topical dermal doses of 150 mcg/kg and above (approximately 3 times the maximum recommended daily inhalation dose in adults on an mcg/m^2 basis). In an oral study, mometasone furoate increased resorptions and caused cleft palate and/or head malformations (hydrocephaly and domed head) at 700 mcg/kg (less than the maximum recommended daily inhalation dose in adults on an area under the curve [AUC] basis). At 2800 mcg/kg (approximately 2 times the maximum recommended daily inhalation dose in adults on an AUC basis) most litters were aborted or resorbed. No toxicity was observed at 140 mcg/kg (less than the maximum recommended daily inhalation dose in adults on an AUC basis).

14 CLINICAL STUDIES

14.1 Asthma

Adults and Adolescents 12 Years of Age and Older: The efficacy of ASMANEX TWISTHALER in patients with asthma 12 years and older was evaluated in ten 8- to 12-week, randomized, double-blind, placebo-controlled, parallel-group clinical trials. These trials included 1750 patients ranging from 12 to 83 years of age; 38% male and 62% female; and 83% Caucasian, 8% black, 6% Hispanic, and 3% other race/ethnicity. Patients received ASMANEX TWISTHALER 110 mcg twice daily (n=133), 220 mcg once daily in the morning (n=209), 220 mcg once daily in the evening (n=232), 220 mcg twice daily (n=433), 440 mcg once daily in the morning (n=419), 440 mcg once daily in the evening (n=250), or 440 mcg twice daily (n=74). The results of the clinical trials are presented based upon previous asthma therapy.

Patients ≥12 Years of Age Previously Maintained on Bronchodilators Alone: ASMANEX TWISTHALER was studied in three 12-week, double-blind trials in 737 patients with mild to moderate asthma (mean baseline FEV1≅2.6 L, 72% of predicted normal) who were maintained on short-acting beta2-agonists alone. The first 2 trials evaluated doses of 440 mcg administered as 2 inhalations once daily in the morning and 1 of these studies also evaluated 220 mcg twice daily. In both trials, morning predose FEV1 was significantly improved at endpoint (last observation) following treatment with 440 mcg ASMANEX TWISTHALER once daily in the morning as compared to placebo (14% vs. 2.5%, respectively, in 1 trial and 16% vs. 5.5% in the other). There was also a significant improvement in morning predose FEV1 at endpoint following treatment with ASMANEX TWISTHALER 220 mcg twice daily. Other measures of lung function (morning and evening PEFR) also showed improvement compared to placebo. Patients receiving ASMANEX TWISTHALER treatment had reduced frequency of beta2-agonist rescue medication use compared to those on placebo (mean reductions at endpoint 2.2 and 0.5 puffs per day, respectively, from a baseline of 4.1 puffs/day). Additionally, fewer patients receiving ASMANEX TWISTHALER 440 mcg once daily experienced asthma worsening than did patients receiving placebo.

In the third trial, 195 asthmatic patients were treated with ASMANEX TWISTHALER 220 mcg once daily in the evening or placebo. The morning FEV1 at endpoint was significantly improved compared to placebo (mean change at endpoint 0.43 L or 16.8% vs. 0.16 L or 6%, respectively, see Figure 1). Evening PEF increased 24.96 L/min (7%) from baseline in the ASMANEX TWISTHALER group compared to 8.67 L/min (4%) in placebo.

Patients ≥12 Years of Age Previously Maintained on Inhaled Corticosteroids: The efficacy and safety of ASMANEX TWISTHALER in doses ranging from 110 mcg twice daily to 440 mcg twice daily was evaluated in 3 trials in 1072 patients previously maintained on inhaled corticosteroids. In the first 2 trials, asthmatic patients (mean baseline FEV1 ~2.6 L, 76% predicted) were previously on either beclomethasone dipropionate [84–1200 mcg/day], flunisolide [100–2000 mcg/day], fluticasone propionate [110–880 mcg/day], or triamcinolone acetonide [300–2400 mcg/day]. The first trial included 307 patients who were treated in an open-label fashion with ASMANEX TWISTHALER 220 mcg (110 mcg × 2 inhalations) twice daily for 2 weeks followed by 12 weeks of double-blind treatment with ASMANEX TWISTHALER 440 mcg once daily in the morning or placebo. The second trial involved 365 patients who continued on their previous dose of inhaled corticosteroids during a 2-week screening period before being switched to ASMANEX TWISTHALER 440 mcg twice daily, 220 mcg twice daily, 110 mcg twice daily, beclomethasone dipropionate 168 mcg twice daily, or placebo for 12 weeks.

In the first trial, morning predose FEV1 was effectively maintained (-1.4% change from baseline to endpoint) over the 12 weeks in the patients who were randomized to ASMANEX TWISTHALER 440 mcg once daily in the morning, while decreasing 10% at endpoint in those switched to placebo. In addition, fewer patients treated with ASMANEX TWISTHALER experienced worsening of asthma compared to placebo.

In the second trial, morning predose FEV1 was significantly increased at endpoint when patients were switched to ASMANEX TWISTHALER 220 mcg twice daily (7% increase) or 440 mcg twice daily (6.2% increase) as compared to a decrease of 7% when switched to placebo. Additionally, beta2-agonist rescue medication use was decreased for patients who received ASMANEX TWISTHALER treatment relative to those on placebo (mean reduction from baseline to endpoint 1.1 puffs/day vs. increase of 0.7 puffs/day). Fewer patients receiving ASMANEX TWISTHALER treatment experienced asthma worsening than did patients receiving placebo.

The third trial evaluated the efficacy and safety of ASMANEX TWISTHALER compared to placebo in 400 asthmatic patients (mean FEV1 67% predicted at baseline) previously maintained on beclomethasone dipropionate (hydrofluoroalkane [HFA] or chlorofluorocarbon [CFC]) 168–600 mcg/day, budesonide 200–1200 mcg/day, flunisolide 500–2000 mcg/day, fluticasone propionate 88–880 mcg/day, or triamcinolone acetonide 400–1600 mcg/day. Following a 28-day inhaled corticosteroid dose-reduction phase, patients were randomized to ASMANEX TWISTHALER 440 mcg once daily in the evening, 220 mcg once daily in the evening, 220 mcg twice daily, or placebo. At endpoint, patients who received ASMANEX TWISTHALER 220 mcg once daily in the evening, 440 mcg once daily in the evening, or 220 mcg twice daily had a significant improvement in morning FEV1 [0.41 L (19%), 0.49 L (22%), and 0.51 L (24%) in the 220 mcg once daily in the evening, 440 mcg once daily in the evening, and 220 mcg twice daily treatment group, respectively] compared to placebo [0.16 L (8%)] (see Figure 2). Evening PEF increased 15.65 L/min (4.1%) with the 220 mcg once daily in the evening dose, 39.26 L/min (10.7%) with the 440 mcg once daily in the evening dose, and 36.7 L/min (10.8%) with the 220 mcg twice daily dose, respectively, compared to a 1.4 L/min (1%) increase with placebo. Patients receiving all doses of ASMANEX TWISTHALER treatment had reduced frequency of beta-agonist rescue medication use compared to those on placebo (mean reductions at endpoint of 1.4–1.8 puffs/day from a baseline of more than 3 puffs/day compared to an increase in use by 0.5 puffs/day for placebo). In addition, fewer patients receiving ASMANEX TWISTHALER experienced asthma worsening than did those on placebo.

Patients ≥12 Years of Age Previously Maintained on Oral Corticosteroids: The efficacy of ASMANEX TWISTHALER 440 mcg and 880 mcg twice daily was evaluated in one 12-week, double-blind trial in patients previously maintained on oral corticosteroids. A total of 132 patients requiring oral prednisone (baseline mean daily oral prednisone requirement approximately 12 mg; baseline FEV1 of 1.8 L, 59% of predicted normal), most of whom were also on inhaled corticosteroids (baseline inhaled steroid: beclomethasone dipropionate [168–840 mcg/day], budesonide [800–1600 mcg/day], flunisolide [1000–2000 mcg/day], fluticasone propionate [440–1760 mcg/day], or triamcinolone acetonide [400–2400 mcg/day]) were studied. Patients who received ASMANEX TWISTHALER 440 mcg twice daily had a significant reduction in their oral prednisone (46%) as compared to placebo (164% increase in oral prednisone dose). Additionally, 40% of patients on ASMANEX TWISTHALER 440 mcg twice daily were able to completely discontinue their use of prednisone, whereas 60% of patients on placebo had an increase in daily prednisone use. Patients on ASMANEX TWISTHALER had significant improvement in lung function (14% increase) compared to a 12% decrease in FEV1 in the placebo group. Additionally, mean rescue beta2-agonist use was reduced to approximately 3 puffs/day from a baseline of 4–5 puffs/day with ASMANEX TWISTHALER treatment, compared to an increase of 0.3 puffs/day on placebo. Patients who received ASMANEX TWISTHALER 880 mcg twice daily experienced no additional benefit beyond that seen with 440 mcg twice daily.

Pediatric Patients 4 to 11 Years of Age: The efficacy of ASMANEX TWISTHALER in patients with asthma 4 to 11 years of age was evaluated in three 12-week, randomized, double-blind, placebo-controlled, parallel-group clinical trials. These trials included 630 patients receiving ASMANEX TWISTHALER, ranging from 4 to 11 years of age; 63% male and 37% female; and 67% Caucasian, 13% black, 17% Hispanic, and 3% other race/ethnicity. Patients received ASMANEX TWISTHALER 110 mcg once daily in the evening (n=98), 110 mcg once daily in the morning (n=181), 110 mcg twice daily (n=179), or 220 mcg once daily in the morning (n=172). The results for 1 clinical trial are described below. The other 2 clinical trials support the efficacy of ASMANEX TWISTHALER.

A 12-week, placebo-controlled trial of 296 patients 4 to 11 years of age with asthma of at least 6 months duration (mean % predicted FEV1 at baseline ranging from 77.3%–79.7%) was conducted to demonstrate the efficacy of the ASMANEX TWISTHALER in the treatment of asthma. Patients were treated with ASMANEX TWISTHALER 110 mcg once daily in the evening (n=98) or placebo (n=99) for 12 weeks. Assessment of efficacy was based upon morning predose FEV1. The primary endpoint was the mean change from baseline to endpoint in percent-predicted FEV1. For the primary endpoint, improvement in the ASMANEX TWISTHALER 110 mcg once daily in the evening treatment group (4.73) was statistically significant compared to placebo (-1.77). Figure 3 displays the results for % predicted FEV1 change from baseline at endpoint.

In this study, secondary endpoints of morning and evening peak expiratory flow and rescue medication use were supportive of efficacy of ASMANEX TWISTHALER.

16 HOW SUPPLIED/STORAGE AND HANDLING

How Supplied

ASMANEX TWISTHALER 220 mcg: delivers 200 mcg mometasone furoate from the mouthpiece

- comprised of an assembled plastic cap–activated dosing mechanism with dose counter, drug-product storage unit, drug-product formulation (135 mg for the 14 and 30 inhalation units and 240 mg for the 60 and 120 inhalation units), and mouthpiece, covered by a white screw cap that bears the product label.
- body of the inhaler is white and the turning grip is pink with a clear plastic window indicating the number of doses remaining. The inhaler will not deliver subsequent doses once the counter reaches zero (“00”).
- 14 inhalation units (Institutional Use Only; NDC# 78206-114-03)
- 30 inhalation units (NDC# 78206-114-04)
- 60 inhalation units (for more than 1 inhalation daily; NDC# 78206-114-02)
- 120 inhalation units (for more than 2 inhalations daily; NDC# 78206-114-01)

ASMANEX TWISTHALER 110 mcg: delivers 100 mcg mometasone furoate from the mouthpiece

- comprised of an assembled plastic cap–activated dosing mechanism with dose counter, drug-product storage unit, drug-product formulation (135 mg), and mouthpiece, covered by a white screw cap that bears the product label.
- body of the inhaler is white and the turning grip is gray with a clear plastic window indicating the number of doses remaining. The inhaler will not deliver subsequent doses once the counter reaches zero (“00”).
- 30 inhalation units (NDC# 78206-115-01)

Each inhaler is supplied in a protective foil pouch with Patient’s Instructions for Use.

Storage and Handling

Store in a dry place at 25°C (77°F); excursions permitted to 15°C to 30°C (59°F to 86°F) [see USP Controlled Room Temperature].

Discard the inhaler 45 days after opening the foil pouch or when dose counter reads "00", whichever comes first.

17 PATIENT COUNSELING INFORMATION

Advise the patient to read the FDA-approved patient labeling (Patient Information and Instructions for Use).

Oropharyngeal Candidiasis

Patients should be advised that localized infections with Candida albicans occurred in the mouth and pharynx in some patients. If oropharyngeal candidiasis develops, it should be treated with appropriate local or systemic (i.e., oral) antifungal therapy while still continuing with ASMANEX TWISTHALER therapy, but at times therapy with ASMANEX TWISTHALER may need to be temporarily interrupted under close medical supervision. Rinsing the mouth after inhalation is advised [see Warnings and Precautions (5.1)].

Acute Asthma Episodes

Patients should be advised that ASMANEX TWISTHALER is not a bronchodilator and should not be used to treat status asthmaticus or to relieve acute asthma symptoms. Acute asthma symptoms should be treated with an inhaled, short-acting beta2-agonist such as albuterol [see Warnings and Precautions (5.2)].

Hypersensitivity Reactions Including Anaphylaxis

Hypersensitivity reactions including rash, pruritus, angioedema and anaphylactic reaction have been reported with use of ASMANEX TWISTHALER. Discontinue ASMANEX TWISTHALER if such reactions occur [see Contraindications (4), Warnings and Precautions (5.3), and Adverse Reactions (6.2)].

ASMANEX TWISTHALER contains small amounts of lactose, which contains trace levels of milk proteins. In postmarketing experience with ASMANEX TWISTHALER, anaphylactic reactions in patients with milk protein allergy have been reported [see Contraindications (4) and Adverse Reactions (6.2)].

Immunosuppression and Risk of Infections

Patients who are on immunosuppressant doses of corticosteroids should be warned to avoid exposure to chickenpox or measles and, if exposed, to consult their physician without delay. Patients should be informed of potential worsening of existing tuberculosis; fungal, bacterial, viral, or parasitic infections; or ocular herpes simplex [see Warnings and Precautions (5.4)].

Hypercorticism and Adrenal Suppression

Patients should be advised that ASMANEX TWISTHALER may cause systemic corticosteroid effects of hypercorticism and adrenal suppression. Additionally, patients should be instructed that deaths due to adrenal insufficiency have occurred during and after transfer from systemic corticosteroids. Patients should taper slowly from systemic corticosteroids if transferring to ASMANEX TWISTHALER [see Warnings and Precautions (5.6)].

Reduction in Bone Mineral Density

Patients who are at an increased risk for decreased BMD should be advised that the use of corticosteroids may pose an additional risk and should be monitored and, where appropriate, be treated for this condition [see Warnings and Precautions (5.7)].

Reduced Growth Velocity

Patients should be informed that orally inhaled corticosteroids, including mometasone furoate inhalation powder, may cause a reduction in growth velocity when administered to pediatric patients. Physicians should closely follow the growth of children and adolescents taking corticosteroids by any route [see Warnings and Precautions (5.8)].

Use Daily for Best Effect

Patients should be advised to use ASMANEX TWISTHALER at regular intervals, since its effectiveness depends on regular use. Maximum benefit may not be achieved for 1 to 2 weeks or longer after starting treatment. If symptoms do not improve in that time frame or if the condition worsens, patients should be instructed to contact their physician.

Instructions for Use

Patients should be instructed to record the date of pouch opening on the cap label and discard the inhaler 45 days after opening the foil pouch or when the dose counter reads "00" and the final dose has been inhaled, whichever comes first. The inhaler should be held upright while removing the cap. The medication should be taken as directed, breathing rapidly and deeply, and patients should not breathe out through the inhaler. The mouthpiece should be wiped dry and the cap replaced immediately following each inhalation and rotated fully until the click is heard. After administration, the patient should rinse their mouth with water and spit out contents without swallowing. Patients should store the unit as instructed. The dose counter displays the doses remaining. When the dose counter indicates zero, the cap will lock and the unit must be discarded. Patients should be advised that if the dose counter is not working correctly, the unit should not be used and it should be brought to their physician or pharmacist.

Manufactured for: Organon LLC, a subsidiary of
ORGANON & Co.,
Jersey City, NJ 07302, USA

Manufactured by:
MSD International GmbH (Singapore Branch)
Singapore 638030, Singapore

For patent information: www.organon.com/our-solutions/patent/

The trademarks above are owned by their respective owners.

Copyright © 2021 Organon Global Inc.
All rights reserved.

uspi-og0887-pwih-2106r001

Patient Information
ASMANEX® TWISTHALER® (AZ-ma-neks)
(mometasone furoate inhalation powder)
for oral inhalation use only

What is ASMANEX TWISTHALER?
ASMANEX TWISTHALER is an inhaled corticosteroid (ICS) prescription medicine used as maintenance treatment for the prevention and control of asthma symptoms in people 4 years of age and older.

- ASMANEX TWISTHALER is not used to treat sudden severe symptoms of asthma.
- ASMANEX TWISTHALER should not be used as a rescue inhaler.
- It is not known if ASMANEX TWISTHALER is safe and effective in children less than 4 years of age.

Do not use ASMANEX TWISTHALER:

- to treat sudden severe symptoms of asthma.
- if you are allergic to milk proteins, mometasone furoate, or any of the ingredients in ASMANEX TWISTHALER. See the end of this Patient Information leaflet for a complete list of ingredients in ASMANEX TWISTHALER.

Before you use ASMANEX TWISTHALER, tell your healthcare provider about all of your medical conditions including if you:

- have liver problems.
- have osteoporosis.
- have an immune system problem.
- have eye problems such as increased pressure in the eye (glaucoma), cataracts, blurred vision, or other changes in your vision.
- are allergic to any medicines.
- are exposed to chickenpox or measles.
- have or have had tuberculosis (TB), any untreated fungal, bacterial or viral infections or parasitic infections, or eye infections caused by herpes.
- are pregnant or planning to become pregnant. It is not known if ASMANEX TWISTHALER may harm your unborn baby.
- are breastfeeding. It is not known if ASMANEX TWISTHALER passes into your breast milk and if it can harm your baby. You and your healthcare provider should decide if you will either take ASMANEX TWISTHALER or breastfeed.

Tell your healthcare provider about all the medicines you take, including prescription and over-the-counter medicines, vitamins, and herbal supplements.
ASMANEX TWISTHALER may affect the way other medicines work, and other medicines may affect how ASMANEX TWISTHALER works.

Especially, tell your healthcare provider if you take antifungal medicines, antibiotic medicines, or anti-HIV medicines such as:

- ritonavir
- atazanavir
- cobicistat-containing products

- ketoconazole
- clarithromycin

- nefazodone
- saquinavir

- nelfinavir
- telithromycin

- indinavir
- itraconazole

Ask your healthcare provider if you are not sure if any of your medicines are the kinds listed above.

For some medicines (including medicines for HIV such as ritonavir, cobicistat-containing products, and certain antifungals and antibiotics) your healthcare provider may wish to monitor you carefully.

Know the medicines you take. Keep a list and show it to your healthcare provider and pharmacist each time you get a new medicine.

How should I use ASMANEX TWISTHALER?
Read the step-by-step instructions for using ASMANEX TWISTHALER in the Instructions for Use.

- Use ASMANEX TWISTHALER exactly as prescribed. Do not use ASMANEX TWISTHALER more often than prescribed.
- You must use ASMANEX TWISTHALER regularly. It may take 1 week to 2 weeks or longer after you start using ASMANEX TWISTHALER for your asthma symptoms to get better. Do not stop using ASMANEX TWISTHALER even if you are feeling better, unless your healthcare provider tells you to.
- Do not change or stop using ASMANEX TWISTHALER or other asthma medicines used to control or threat your breathing problems unless told to do so by your healthcare provider. Your healthcare provider will change your medicines as needed.
- ASMANEX TWISTHALER comes in 2 strengths. Your healthcare provider has prescribed the strength that is best for you. Pay attention to the differences between ASMANEX TWISTHALER and your other inhaled medicines, including their prescribed use and the way they look.
- ASMANEX TWISTHALER gives the medicine in a fine powder that you or your child may not taste, smell, or feel.
- If you take more ASMANEX TWISTHALER than your healthcare provider has prescribed, call your healthcare provider right away.
- ASMANEX TWISTHALER does not relieve sudden asthma symptoms. Always have a rescue inhaler such as albuterol with you to treat sudden symptoms. Use your rescue inhaler if you have breathing problems between doses of ASMANEX TWISTHALER. If you do not have a rescue inhaler such as albuterol, call your healthcare provider to have a rescue inhaler prescribed for you.
- Rinse your mouth with water after each dose of ASMANEX TWISTHALER. Spit out the water. Do not swallow it. This will help lessen the chance of getting a yeast infection (thrush) in your mouth and throat.
- Call your healthcare provider or get medical care right away if you have asthma and your symptoms do not improve after using ASMANEX TWISTHALER regularly for 1 to 2 weeks.
- Do not use the ASMANEX TWISTHALER if the inhaler or any of its parts are not working properly. Take it to your healthcare provider or pharmacist.

What are the possible side effects of ASMANEX TWISTHALER?
ASMANEX TWISTHALER can cause serious side effects, including:

- Thrush in your mouth and throat. This is a serious but common side effect. You may develop thrush, a yeast (Candida albicans), in your mouth or throat. After each dose of ASMANEX TWISTHALER, rinse your mouth with water. Spit out the water. Do not swallow it. This will help to prevent thrush in your mouth or throat.
- Increased wheezing right after taking ASMANEX TWISTHALER. Always have a rescue inhaler with you to treat sudden wheezing.
- Serious allergic reactions. Stop taking ASMANEX TWISTHALER and call your healthcare provider or get emergency medical care right away if you get any of the following symptoms of a serious allergic reaction:

- rash

- itching

- swelling, including swelling of the face, mouth, and tongue

- breathing problems

- Immune system effects and a higher chance for infections. You are more likely to get infections if you take medicines that weaken your immune system. Avoid contact with people who have contagious diseases such as chicken pox or measles while using ASMANEX TWISTHALER.
  Tell your healthcare provider about any signs of infection such as:

- fever

- feeling tired

- body aches

- vomiting

- pain

- nausea

- chills

- Adrenal insufficiency that can lead to death can happen when you stop taking oral corticosteroid medicines and start using inhaled corticosteroid medicines. Adrenal insufficiency can also happen in people who take higher doses of ASMANEX TWISTHALER than recommended over a long period of time. When your body is under stress such as from fever, trauma (such as a car accident), infection, or surgery, adrenal insufficiency can get worse. Symptoms of adrenal insufficiency include:

- feeling tired or exhausted (fatigue)
- weakness

- lack of energy
- nausea and vomiting

- low blood pressure (hypotension)
- dizziness or feeling faint

- Lower bone mineral density. This may be a problem for people who already have a higher chance for low bone density (osteoporosis).
- Slowed growth in children. A child’s growth should be checked often.
- Eye problems including glaucoma, cataracts, and blurred vision. You should have regular eye exams while using ASMANEX TWISTHALER.

The most common side effects reported while using ASMANEX TWISTHALER include:

- headache
- painful menstrual periods
- sinus infection
- upper respiratory tract infection
- upset stomach

- muscle and bone pain
- back pain
- nasal allergy symptoms
- sore throat

Other side effects: Worsening asthma or sudden asthma attacks have been reported with the use of inhaled mometasone furoate.
Tell your healthcare provider about any side effect that bothers you or that does not go away.
These are not all the side effects with ASMANEX TWISTHALER. Ask your healthcare provider or pharmacist for more information. Call your doctor for medical advice about side effects. You may report side effects to FDA at 1-800-FDA-1088.

General information about the safe and effective use of ASMANEX TWISTHALER.
Medicines are sometimes prescribed for purposes other than those listed in a Patient Information leaflet. Do not use ASMANEX TWISTHALER for a condition for which it was not prescribed. Do not give your ASMANEX TWISTHALER to other people, even if they have the same condition that you have. It may harm them.
You can ask your healthcare provider or pharmacist for information about ASMANEX TWISTHALER that was written for healthcare professionals.
For more information about ASMANEX TWISTHALER go to www.ASMANEX.com or to report side effects call 1-844-674-3200.

What are the ingredients in ASMANEX TWISTHALER?
Active ingredient: mometasone furoate
Inactive ingredient: anhydrous lactose (which contains trace amounts of milk proteins).

This Patient Information has been approved by the U.S. Food and Drug Administration.

Revised Date: 6/2021

Instructions for Use
ASMANEX® TWISTHALER® (AZ-ma-neks)
(mometasone furoate inhalation powder)
for oral inhalation use only

It is important that you read this information as the ASMANEX TWISTHALER may work differently from inhalers you have used before.
Read this Instructions for Use before you start using ASMANEX TWISTHALER and each time you get a refill. There may be new information. This information does not take the place of talking to your healthcare provider about your medical condition or treatment.

TWISTHALER Parts:
See Figures A and B below to become familiar with the TWISTHALER parts.

- Remove the ASMANEX TWISTHALER from its foil pouch and write the date on the cap label.

- Follow Steps 1 and 2 below each time you inhale a dose from your ASMANEX TWISTHALER.

Step 1: Open TWISTHALER

Hold the TWISTHALER straight up (upright position) with the colored portion (the base) on the bottom (see Figure C). It is important that you remove the cap of the TWISTHALER while it is in this upright position to make sure that you get the right amount of medicine with each dose.

Holding the colored base, twist the cap in a counterclockwise direction to remove it (see Figure C). As you lift off the cap, the dose counter on the base will count down by one. Removing the cap loads the TWISTHALER with the medicine that you are now ready to inhale.

Important: The indented arrow (located on the white portion of the TWISTHALER, directly above the colored base) should now be pointing to the dose counter below. (see Figure C).

Step 2: Inhale dose

- Breathe out fully.
- Bring the TWISTHALER up to your mouth or your child’s mouth with the mouthpiece facing toward you or your child.
- Place the mouthpiece in your mouth or your child’s mouth, holding it in a horizontal (on its side) position as shown below (see Figure D).
- Firmly close your lips around the mouthpiece and take in a fast, deep breath. Since the medicine is a very fine powder, you may not be able to taste, smell, or feel it after inhalation.
- Do not cover the ventilation holes while inhaling the dose.

Step 3: Hold breath

- Remove the TWISTHALER from your mouth and hold your breath for about 10 seconds, or as long as you comfortably can.

Important: Do not breathe out (exhale) into the TWISTHALER.

Step 4: Replace Cap and Close TWISTHALER

- After you take your medicine, it is important that you wipe the mouthpiece dry, if needed, and then replace the cap right away, firmly closing the TWISTHALER right away (see Figures E and F).

Be sure that the indented arrow is in line with the dose counter. Put the cap back onto the TWISTHALER and turn it in a clockwise direction, as you gently press down. You will hear a "click" to let you know that the cap is fully closed. This is the only way to be sure that your next dose is loaded the right way.

Step 5: Rinse mouth

- After using your TWISTHALER, rinse your mouth with water. Spit out the water. Do not swallow it.

How should I clean and store the ASMANEX TWISTHALER?

- Store ASMANEX TWISTHALER at room temperature between 68°F to 77°F (20°C to 25°C).
- Keep dry. Avoid contact with liquids.
- Do not wash the ASMANEX TWISTHALER.
- Clean mouthpiece if needed by gently wiping with a dry cloth or tissue.
- Throw away the ASMANEX TWISTHALER 45 days after opening the foil pouch or when the dose counter reads “00” and you have inhaled the final dose, whichever comes first.
- Keep the ASMANEX TWISTHALER and all medicines out of the reach of children.

How to know when the ASMANEX TWISTHALER is empty.

- The TWISTHALER has a dose counter on the colored base, which shows the number of doses left to use.
- As you lift off the cap to take your dose, the dose counter on the base will count down by 1 (if you began with the dose counter reading “30” this will cause the dose counter to now read “29”).
- Read the numbers from top to bottom.
- When the unit reads “01” this means this is the last dose.
- After dose “01” the counter will read “00”.
- When you replace the cap, the unit will lock and then must be thrown away.
- Start using a new ASMANEX TWISTHALER as instructed by your healthcare provider.

This Instructions for Use has been approved by the U.S. Food and Drug Administration

Manufactured for: Organon LLC, a subsidiary of
ORGANON & Co.,
Jersey City, NJ 07302, USA

Manufactured by:
MSD International GmbH (Singapore Branch)
Singapore 638030, Singapore

For patent information: www.organon.com/our-solutions/patent/

The trademarks above are owned by their respective owners.

Copyright © 2021 Organon Global Inc.
All rights reserved.

Revised: 6/2021

usppi-og0887-pwih-2106r001

PRINCIPAL DISPLAY PANEL - 220 mcg - 120 Dose Inhaler Pouch Carton

NDC 78206-114-01

For Oral Inhalation
Rx only

Asmanex®
Twisthaler®
mometasone furoate inhalation powder
220 mcg per actuation

120 Metered Doses
(For more than 2 inhalations daily)

Discard Twisthaler inhaler 45 days after
opening foil pouch or when dose counter
reads "00", whichever comes first.

Attention Pharmacist: Detach Patient's
Instructions for Use and dispense with inhaler

PRINCIPAL DISPLAY PANEL - 110 mcg - 30 Dose Inhaler Pouch Carton

NDC 78206-115-01

For Oral Inhalation
Rx only

Asmanex®
Twisthaler®
mometasone furoate inhalation powder
110 mcg per actuation

Usual Dose for 4 to 11 years of age is 110 mcg

30 Metered Doses

Discard Twisthaler inhaler 45 days after
opening foil pouch or when dose counter
reads "00", whichever comes first.

Attention Pharmacist: Detach Patient's
Instructions for Use and dispense with inhaler